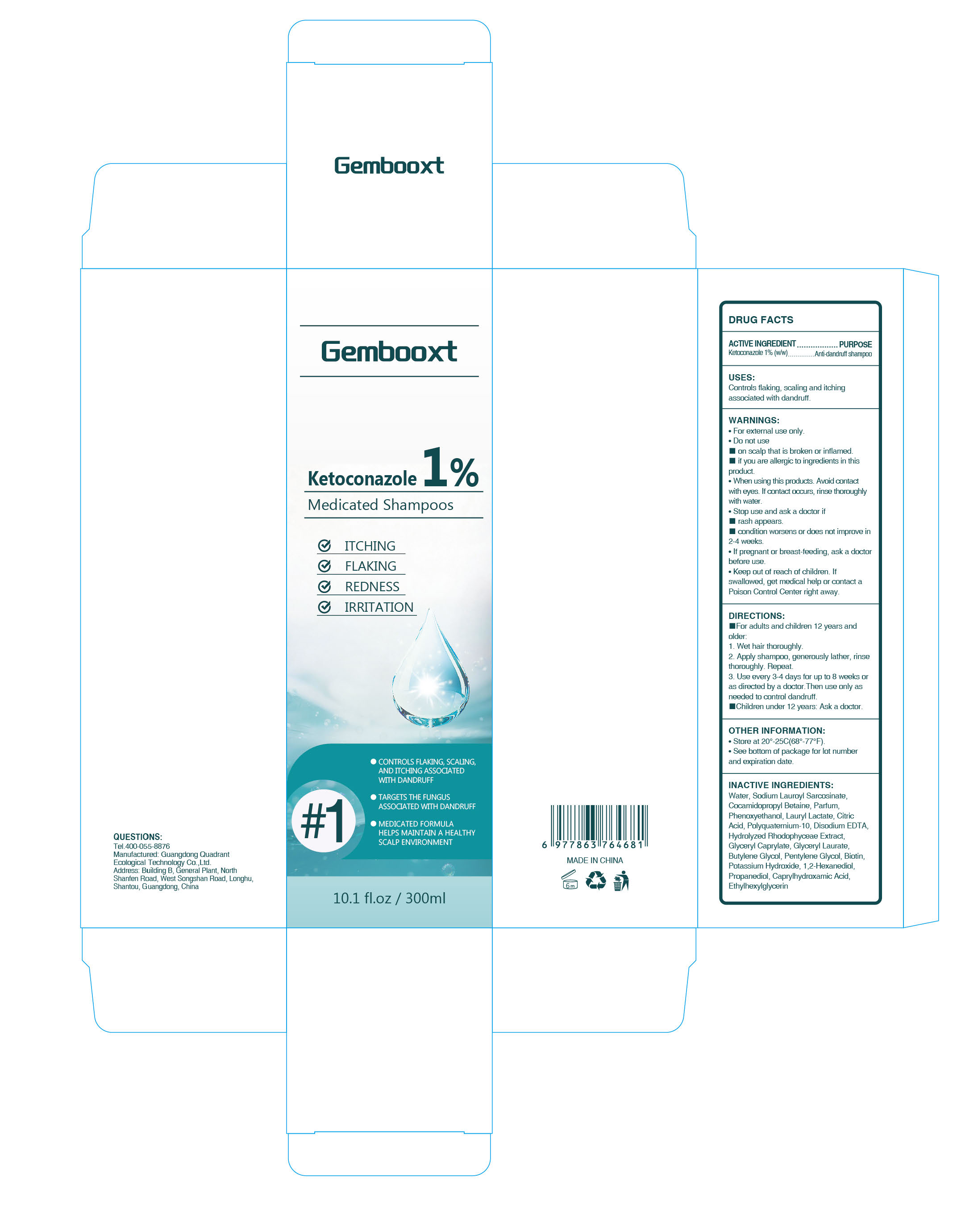 DRUG LABEL: Gembooxt Ketoconazole 1% Medicated Shampoos
NDC: 76986-025 | Form: LIQUID
Manufacturer: Guangdong Quadrant Ecological Technology Co., Ltd.
Category: otc | Type: HUMAN OTC DRUG LABEL
Date: 20260130

ACTIVE INGREDIENTS: KETOCONAZOLE 0.01 g/1 mL
INACTIVE INGREDIENTS: LAURYL LACTATE; COCAMIDOPROPYL BETAINE; GLYCERYL CAPRYLATE; WATER; PENTYLENE GLYCOL; BIOTIN; 1,2-HEXANEDIOL; ETHYLHEXYLGLYCERIN; PROPANEDIOL; POTASSIUM HYDROXIDE; GLYCERYL LAURATE; CAPRYLHYDROXAMIC ACID; SODIUM LAUROYL SARCOSINATE; PHENOXYETHANOL; CITRIC ACID; POLYQUATERNIUM-10 (1000 MPA.S AT 2%); EDETATE DISODIUM; BUTYLENE GLYCOL

76986-025 Gembooxt Ketoconazole 1% Medicated Shampoos

ACTIVE INGREDIENT

Ketoconazole 1%

PURPOSE

Anti-dandruff shampoo

INDICATIONS AND USAGE

Controls flaking, scaling and itching associated with dandruff

WARNINGS

For external use only.

DO NOT USE

on scalp that is broken or inflamed.
if you are allergic to ingredients in this product.

WHEN USING

When using this products. Avoid contact with eyes. lf contact occurs, rinse thoroughly with water.
If pregnant or breast-feeding, ask a doctor before use.

STOP USE

rash appears.
condition worsens or does not improve in 2-4 weeks.

Keep out of reach of children. lf swallowed, get medical help or contact a Poison Control Center right away.

DOSAGE AND ADMINISTRATION

For adults and children 12 years and older:
1. Wet hair thoroughly.
2. Apply shampoo, generously lather, rinse thoroughly. Repeat.
3. Use every 3-4 days for up to 8 weeks or as directed by a doctor.Then use only as needed to control dandruff.
Children under 12 years: Ask a doctor.

INACTIVE INGREDIENT

WATER
SODIUM LAUROYL SARCOSINATE
COCAMIDOPROPYL BETAINE
WATER
PARFUM
GLYCERYL CAPRYLATE
GLYCERYL LAURATE
PHENOXYETHANOL
WATER
LAURYL LACTATE
CITRIC ACID
POLYQUATERNIUM-10
DISODIUM EDTA
HYDROLYZED RHODOPHYCEAE EXTRACT
BUTYLENE GLYCOL
1,2-HEXANEDIOL
PENTYLENE GLYCOL
PROPANEDIOL
CAPRYLHYDROXAMIC ACID
ETHYLHEXYLGLYCERIN
BIOTIN
POTASSIUM HYDROXIDE